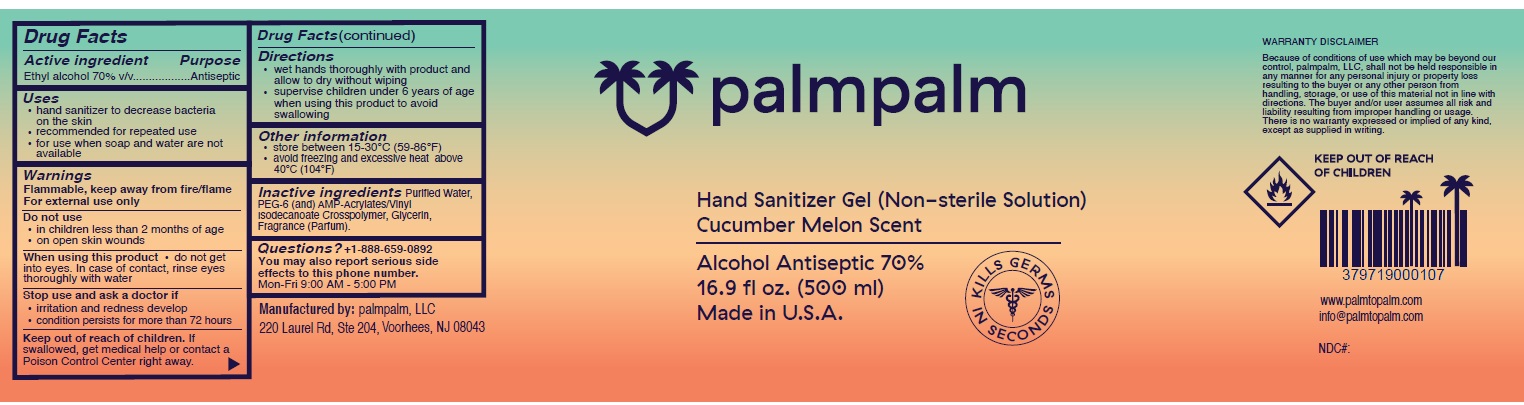 DRUG LABEL: palmpalm Hand Sanitizer
NDC: 79719-100 | Form: GEL
Manufacturer: PALMPALM, LLC
Category: otc | Type: HUMAN OTC DRUG LABEL
Date: 20200817

ACTIVE INGREDIENTS: ALCOHOL 70 mL/100 mL
INACTIVE INGREDIENTS: WATER; POLYETHYLENE GLYCOL 300; ACRYLATES/VINYL ISODECANOATE CROSSPOLYMER (10000 MPA.S NEUTRALIZED AT 0.5%); GLYCERIN

palmpalm Hand Sanitizer Gel

Active ingredient

Ethyl alcohol 70% v/v

Purpose

Antiseptic

Uses

- hand sanitizer to decrease bacteria on the skin
- recommended for repeated use
- for use when soap and water are not available

Warnings

Flammable, keep away from fire/flame
For external use only

Do not use

- in children less than 2 months of age
- on open skin wounds

When using this product • do not get into eyes. In case of contact, rinse eyes thoroughly with water

Stop use and ask a doctor if

- irritation and redness develop
- condition persists for more than 72 hours

Keep out of reach of children. If swallowed, get medical help or contact a Poison Control Center right away.

Directions

- wet hands thoroughly with product and allow to dry without wiping
- supervise children under 6 years of age when using this product to avoid swallowing

Other information

- store between 15-30°C (59-86°F)
- avoid freezing and excessive heat above 40°C (104°F)

Inactive ingredients

Purified Water, PEG-6 (and) AMP-Acrylates/Vinyl Isodecanoate Crosspolymer, Glycerin, Fragrance (Parfum).

Questions?

+1-888-659-0892
You may also report serious side effects to this phone number.
Mon-Fri 9:00 AM - 5:00 PM

Non-sterile Solution

Cucumber Melon Scent

Made in U.S.A.

KILLS GERMS IN SECONDS

WARRANTY DISCLAIMER
Because of conditions of use which may be beyond our control, palmpalm, LLC, shall not be held responsible in any manner for any personal injury or property loss resulting to the buyer or any other person from handling, storage, or use of this material not in line with directions. The buyer and/or user assumes all risk and liability resulting from improper handling or usage. There is no warranty expressed or implied of any kind, except as supplied in writing.

www.palmtopalm.com

info@palmtopalm.com

Manufactured by: palmpalm, LLC 220 Laurel Rd, Ste 204, Voorhees, NJ 08043